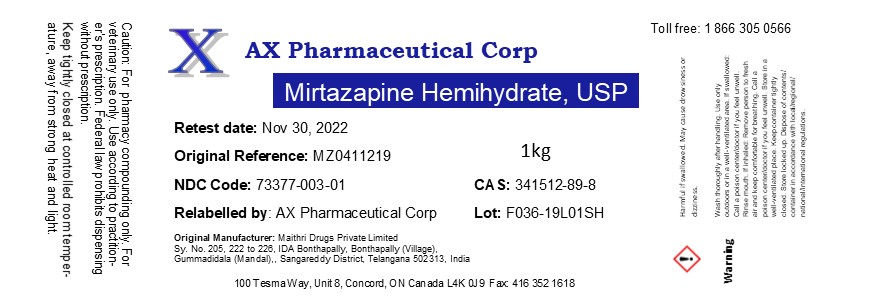 DRUG LABEL: Mirtazapine Hemihydrate
NDC: 73377-003 | Form: POWDER
Manufacturer: AX Pharmaceutical Corp
Category: other | Type: BULK INGREDIENT - ANIMAL DRUG
Date: 20260116

ACTIVE INGREDIENTS: MIRTAZAPINE HEMIHYDRATE 1 kg/1 kg

Mirtazapine Hemihydrate